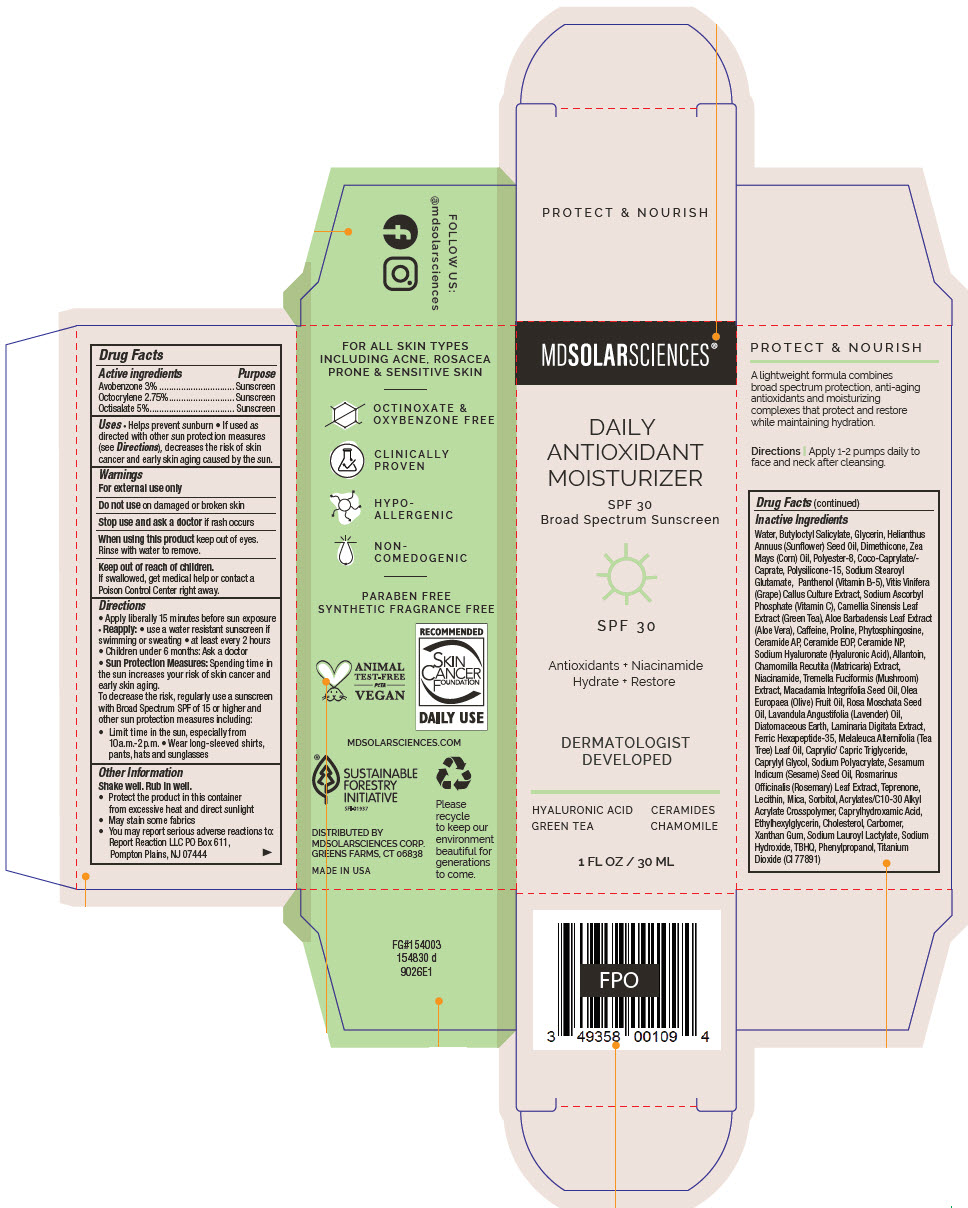 DRUG LABEL: Daily Antioxidant Moisturizer SPF 30. 
NDC: 49358-580 | Form: LOTION
Manufacturer: MDSolarSciences
Category: otc | Type: HUMAN OTC DRUG LABEL
Date: 20230919

ACTIVE INGREDIENTS: Avobenzone 30 mg/1 mL; Octocrylene 27.5 mg/1 mL; Octisalate 50 mg/1 mL
INACTIVE INGREDIENTS: Water; Butyloctyl Salicylate; Glycerin; HELIANTHUS ANNUUS FLOWERING TOP; Dimethicone; CORN OIL; POLYESTER-8 (1400 MW, CYANODIPHENYLPROPENOYL CAPPED); COCOYL CAPRYLOCAPRATE; Polysilicone-15; Sodium Stearoyl Glutamate; PANTHENOL; VITIS VINIFERA SEED; SODIUM ASCORBYL PHOSPHATE; GREEN TEA LEAF; ALOE VERA LEAF; Caffeine; Proline; Phytosphingosine; Ceramide AP; CERAMIDE 9; Ceramide NP; HYALURONATE SODIUM; Allantoin; CHAMOMILE; Niacinamide; TREMELLA FUCIFORMIS FRUITING BODY; MACADAMIA OIL; OLIVE OIL; Rosa Moschata Seed Oil; LAVENDER OIL; Diatomaceous Earth; LAMINARIA DIGITATA; ACETYL HEXAPEPTIDE-8; TEA TREE OIL; MEDIUM-CHAIN TRIGLYCERIDES; Caprylyl Glycol; SODIUM POLYACRYLATE (8000 MW); SESAME OIL; ROSEMARY; Teprenone; HYDROGENATED SOYBEAN LECITHIN; Mica; Sorbitol; CARBOMER INTERPOLYMER TYPE A (ALLYL SUCROSE CROSSLINKED); Caprylhydroxamic Acid; Ethylhexylglycerin; Cholesterol; CARBOMER HOMOPOLYMER TYPE C (ALLYL PENTAERYTHRITOL CROSSLINKED); Xanthan Gum; SODIUM LAUROYL LACTYLATE; Sodium Hydroxide; TERT-BUTYLHYDROQUINONE; PHENYLPROPANOL; TITANIUM DIOXIDE

Daily Antioxidant Moisturizer SPF 30.
SPF 30 Broad Spectrum Sunscreen UVA-UVB

Drug Facts

ACTIVE INGREDIENT

Active ingredients | Purpose
Avobenzone 3% | Sunscreen
Octocrylene 2.75% | Sunscreen
Octisalate 5% | Sunscreen

Uses

- Helps prevent sunburn
- If used as directed with other sun protection measures (see Directions), decreases the risk of skin cancer and early skin aging caused by the sun.

Warnings

For external use only

Do not use on damaged or broken skin

Stop use and ask a doctor if rash occurs

When using this product keep out of eyes. Rinse with water to remove.

Keep out of reach of children.

If swallowed, get medical help or contact a Poison Control Center right away.

Directions

- Apply liberally 15 minutes before sun exposure
- Reapply:
  - use a water resistant sunscreen if swimming or sweating
  - at least every 2 hours
- Children under 6 months: Ask a doctor
- Sun Protection Measures: Spending time in the sun increases your risk of skin cancer and early skin aging.
  To decrease the risk, regularly use a sunscreen with Broad Spectrum SPF of 15 or higher and other sun protection measures including:
  - Limit time in the sun, especially from 10a.m.-2p.m.
  - Wear long-sleeved shirts, pants, hats and sunglasses

Other Information

Shake well. Rub in well.

- Protect the product in this container from excessive heat and direct sunlight
- May stain some fabrics
- You may report serious adverse reactions to:
  Report Reaction LLC PO Box 611,
  Pompton Plains, NJ 07444

Inactive Ingredients

Water, Butyloctyl Salicylate, Glycerin, Helianthus Annuus (Sunflower) Seed Oil, Dimethicone, Zea Mays (Corn) Oil, Polyester-8, Coco-Caprylate/-Caprate, Polysilicone-15, Sodium Stearoyl Glutamate, Panthenol (Vitamin B-5), Vitis Vinifera (Grape) Callus Culture Extract, Sodium Ascorbyl Phosphate (Vitamin C), Camellia Sinensis Leaf Extract (Green Tea), Aloe Barbadensis Leaf Extract (Aloe Vera), Caffeine, Proline, Phytosphingosine, Ceramide AP, Ceramide EOP, Ceramide NP, Sodium Hyaluronate (Hyaluronic Acid), Allantoin, Chamomilla Recutita (Matricaria) Extract, Niacinamide, Tremella Fuciformis (Mushroom) Extract, Macadamia Integrifolia Seed Oil, Olea Europaea (Olive) Fruit Oil, Rosa Moschata Seed Oil, Lavandula Angustifolia (Lavender) Oil, Diatomaceous Earth, Laminaria Digitata Extract, Ferric Hexapeptide-35, Melaleuca Alternifolia (Tea Tree) Leaf Oil, Caprylic/ Capric Triglyceride, Caprylyl Glycol, Sodium Polyacrylate, Sesamum Indicum (Sesame) Seed Oil, Rosmarinus Officinalis (Rosemary) Leaf Extract, Teprenone, Lecithin, Mica, Sorbitol, Acrylates/C10-30 Alkyl Acrylate Crosspolymer, Caprylhydroxamic Acid, Ethylhexylglycerin, Cholesterol, Carbomer, Xanthan Gum, Sodium Lauroyl Lactylate, Sodium Hydroxide, TBHQ, Phenylpropanol, Titanium Dioxide (CI 77891)

DISTRIBUTED BY
MDSOLARSCIENCES CORP.
GREENS FARMS, CT 06838

PRINCIPAL DISPLAY PANEL - 30 ML Bottle Carton

MDSOLARSCIENCES®

DAILY
ANTIOXIDANT
MOISTURIZER

SPF 30
Broad Spectrum Sunscreen

SPF 3 0

Antioxidants + Niacinamide
Hydrate + Restore

DERMATOLOGIST
DEVELOPED

HYALURONIC ACID
GREEN TEA

CERAMIDES
CHAMOMILE

1 FL OZ / 30 ML